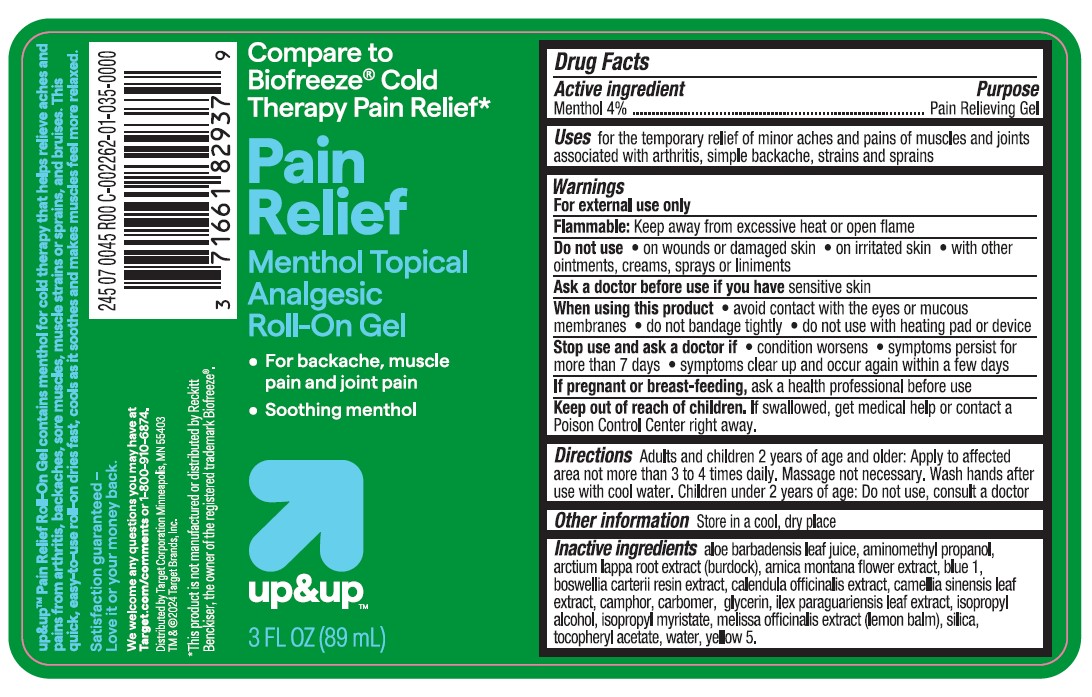 DRUG LABEL: Target Up and Up Pain Relief Menthol Topical Analgesic Roll-On
NDC: 11673-261 | Form: GEL
Manufacturer: TARGET CORPORATION
Category: otc | Type: HUMAN OTC DRUG LABEL
Date: 20240122

ACTIVE INGREDIENTS: MENTHOL, UNSPECIFIED FORM 40 mg/1 mL
INACTIVE INGREDIENTS: ALOE VERA LEAF; ARCTIUM LAPPA ROOT; ARNICA MONTANA FLOWER; FRANKINCENSE; CALENDULA OFFICINALIS FLOWER; GREEN TEA LEAF; CARBOMER INTERPOLYMER TYPE A (ALLYL SUCROSE CROSSLINKED); GLYCERIN; ILEX PARAGUARIENSIS LEAF; ISOPROPYL ALCOHOL; ISOPROPYL MYRISTATE; MELISSA OFFICINALIS LEAF; SILICON DIOXIDE; .ALPHA.-TOCOPHEROL ACETATE; FD&C BLUE NO. 1; WATER; CAMPHOR (SYNTHETIC); AMINOMETHYLPROPANOL; FD&C YELLOW NO. 5

Target Up and Up Pain Relief Menthol Topical Analgesic Roll-On Gel

Active ingredient

Menthol 4%

Purpose

Pain Relieving Gel

Uses

for temporarily relief of minor aches and pains of muscles and joints associated with arthritis, simple backache, strains and sprains

Warnings

For external use only.

Flammable: Keep away from excessive heat or open flame

Do not use

- on wounds or damaged skin
- on irritated skin
- with other ointments, creams, sprays, or liniments

Ask a doctor before use if you have

sensitive skin

When using this product

- avoid contact with the eyes or on mucous membranes
- do not bandage tightly
- do not use with heating pad or device

Stop use and ask a doctor if

- condition worsens
- symptoms persist for more than 7 days
- symptoms clear up and occur again within a few days

If pregnant or breast-feeding,

ask a health professional before use.

Keep out of reach of children.

If swallowed, get medical help or contact a Poison Control Center right away.

Directions

Adults and children 2 years of age and older: Apply to affected area not more than 3 to 4 times daily. Massage not necessary. Wash hands after use with cool water. Children under 2 years of age: Do not use, consult a doctor

Other information

Store in a cool dry place

Inactive ingredients

Aloe Barbadensis Leaf Extract, Aminomethyl Propanol, Arctium Lappa Root (Burdock) Extract, Arnica Montana Flower Extract, Blue 1, Boswellia Carterii Resin Extract, Calendula Officinalis Extract, Camellia Sinensis Leaf Extract, Camphor, Carbomer, Glycerin, Ilex Paraguariensis Leaf Extract, Isopropyl Alcohol, Isopropyl Myristate, Melissa Officinalis (Lemon Balm) Leaf Extract, Silica, Tocopheryl Acetate, Water, Yllow 5.